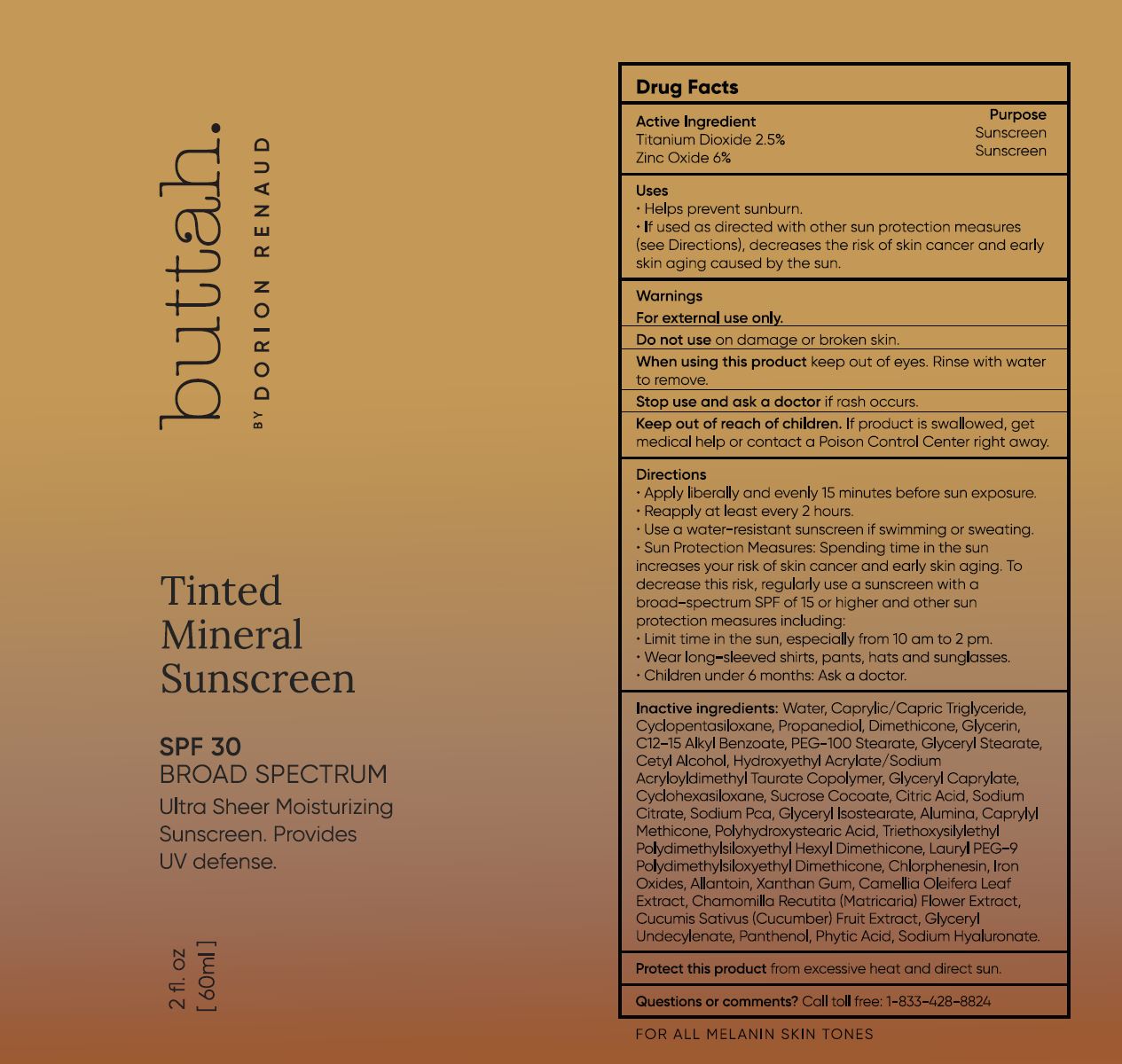 DRUG LABEL: buttah Tinted Mineral Sunscreen
NDC: 82069-102 | Form: LOTION
Manufacturer: Buttah Enterprises, LLC.
Category: otc | Type: HUMAN OTC DRUG LABEL
Date: 20251110

ACTIVE INGREDIENTS: ZINC OXIDE 6 g/100 mL; TITANIUM DIOXIDE 2.5 g/100 mL
INACTIVE INGREDIENTS: WATER; MEDIUM-CHAIN TRIGLYCERIDES; CYCLOMETHICONE 5; PROPANEDIOL; DIMETHICONE; GLYCERIN; ALKYL (C12-15) BENZOATE; PEG-100 STEARATE; GLYCERYL MONOSTEARATE; CETYL ALCOHOL; HYDROXYETHYL ACRYLATE/SODIUM ACRYLOYLDIMETHYL TAURATE COPOLYMER (45000 MPA.S AT 1%); GLYCERYL CAPRYLATE; CYCLOMETHICONE 6; SUCROSE COCOATE; ANHYDROUS CITRIC ACID; SODIUM CITRATE; SODIUM PYRROLIDONE CARBOXYLATE; GLYCERYL ISOSTEARATE; ALUMINUM OXIDE; CAPRYLYL TRISILOXANE; POLYHYDROXYSTEARIC ACID (2300 MW); DIMETHICONE 100; LAURYL PEG-9 POLYDIMETHYLSILOXYETHYL DIMETHICONE; CHLORPHENESIN; FERRIC OXIDE RED; FERRIC OXIDE YELLOW; ALLANTOIN; XANTHAN GUM; GREEN TEA LEAF; MATRICARIA RECUTITA FLOWERING TOP; CUCUMBER; GLYCERYL 1-UNDECYLENATE; PANTHENOL; FYTIC ACID; HYALURONATE SODIUM

BUTTAH- TINTED MINERAL SUNSCREEN 82069-102

ACTIVE INGREDIENTS

TITANIUM DIOXIDE 2.5%

ZINC OXIDE 6%

PURPOSE

Sunscreen

USES

- helps prevent sunburn
- if used as directed with other sun protection measures (see Directions), decreases the risk of skin cancer and early skin aging caused by the sun

WARNINGS

FOR EXTERNAL USE ONLY

DO NOT USE ON DAMAGE OR BROKEN SKIN.

WHEN USING THIS PRODUCT KEEP OUT OF EYES. RINSE WITH WATER TO REMOVE.

STOP USE AND ASK A DOCTOR IF RASH OCCURS.

Keep out of reach of children. If product is swallowed, get medical help or contact Poison Control Center right away.

DIRECTIONS

- APPLY LIBERALLY AND EVENLY 15 MINUTES BEFORE SUN EXPOSURE
- REAPPLY AT LEAST EVERY 2 HOURS.
- USE A WATER-RESISTANT SUNSCREEN IF SWIMMING OR SWEATING.
- SUN PROTECTION MEASURES: SPENDING TIME IN THE SUN INCREASES YOUR RISK OF SKIN CANCER AND EARLY SKIN AGING. TO DECREASE THIS RISK, REGULARLY USE A SUNSCREEN WITH A BROAD-SPECTRUM SPF OF 15 OR HIGHER AND OTHER SUN PROTECTION MEASURES INCLUDING:
- LIMIT TIME IN THE SUN, ESPECIALLY FROM 10 AM TO 2 PM.
- WEAR LONG-SLEEVED SHIRTS, PANTS, HATS, AND SUNGLASSES.
- CHILDREN UNDER 6 MONTHS: ASK A DOCTOR.

INACTIVE INGREDIENTS

Water (Aqua), Caprylic/Capric Triglyceride, Cyclopentasiloxane, Propanediol, Dimethicone, Glycerin, C12-15 Alkyl Benzoate, PEG-100 Stearate, Glyceryl STearate, Cetyl Alcohol, Hydroxyethyl Acrylate/Sodium Acryloyldimethyl Taurate Copolymer, Glyceryl Caprylate, Cyclohexasiloxane, Sucrose Cocoate, Citric Acid, Sodium Citrate, Sodium PCA, Glyceryl Isostearate, Alumina, Caprylyl Methicone, Polyhydroxystearic Acid, Triethoxysilylethyl Polydimethylsiloxyethyl Dimethicone, Chlorphenesin, Iron Oxides, Allantoin, Xanthan Gum, Camellia Oleifera Leaf Extract, Chamomilla Recutita (Matricaria) Flower Extract, Cucumis Sativus (Cucumber) Fruit Extract, Glyceryl Undecylenate, Panthenol, Phytic Acid, Sodium Hyaluronate.

STORAGE AND HANDLING

CALL TOLL FREE: 1-800-428-8824

QUESTIONS OR COMMENTS

- call toll free: 1-833-428-8824